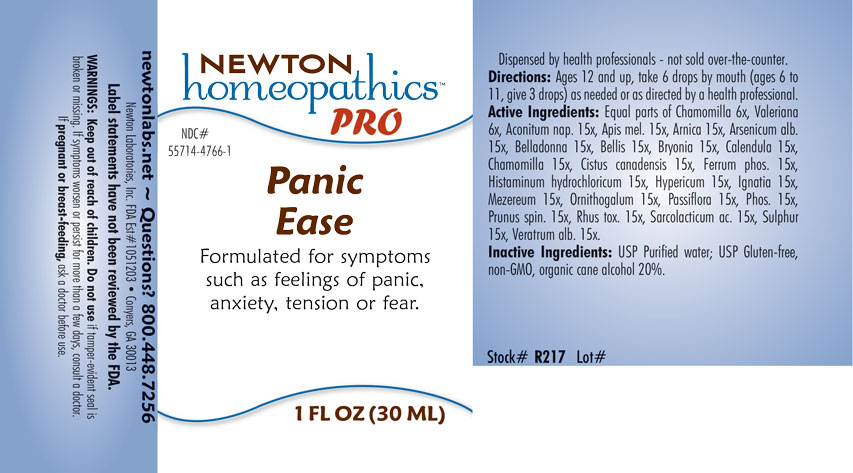 DRUG LABEL: Panic Ease
NDC: 55714-4766 | Form: LIQUID
Manufacturer: Newton Laboratories, Inc.
Category: homeopathic | Type: HUMAN OTC DRUG LABEL
Date: 20250923

ACTIVE INGREDIENTS: ACONITUM NAPELLUS 15 [hp_X]/1 mL; APIS MELLIFERA 15 [hp_X]/1 mL; ARNICA MONTANA 15 [hp_X]/1 mL; ARSENIC TRIOXIDE 15 [hp_X]/1 mL; ATROPA BELLADONNA 15 [hp_X]/1 mL; BELLIS PERENNIS 15 [hp_X]/1 mL; BRYONIA ALBA ROOT 15 [hp_X]/1 mL; CALENDULA OFFICINALIS FLOWERING TOP 15 [hp_X]/1 mL; MATRICARIA CHAMOMILLA 15 [hp_X]/1 mL; HELIANTHEMUM CANADENSE 15 [hp_X]/1 mL; FERROSOFERRIC PHOSPHATE 15 [hp_X]/1 mL; HISTAMINE DIHYDROCHLORIDE 15 [hp_X]/1 mL; HYPERICUM PERFORATUM 15 [hp_X]/1 mL; STRYCHNOS IGNATII SEED 15 [hp_X]/1 mL; DAPHNE MEZEREUM BARK 15 [hp_X]/1 mL; ORNITHOGALUM UMBELLATUM 15 [hp_X]/1 mL; PASSIFLORA INCARNATA FLOWERING TOP 15 [hp_X]/1 mL; PHOSPHORUS 15 [hp_X]/1 mL; PRUNUS SPINOSA FLOWER BUD 15 [hp_X]/1 mL; TOXICODENDRON PUBESCENS LEAF 15 [hp_X]/1 mL; LACTIC ACID, L- 15 [hp_X]/1 mL; SULFUR 15 [hp_X]/1 mL; VERATRUM ALBUM ROOT 15 [hp_X]/1 mL; VALERIAN 6 [hp_X]/1 mL
INACTIVE INGREDIENTS: ALCOHOL; WATER

Panic 4766L

INDICATIONS & USAGE SECTION

Formulated for symptoms such as fellings of panic, anxiety, tension or fear.

DOSAGE & ADMINISTRATION SECTION

Directions: Ages 12 and up, take 6 drops by mouth (ages 0 to 11, give 3 drops) as needed or as directed by a health professional.

OTC - ACTIVE INGREDIENT SECTION

Equal parts of Chamomilla 6x, Valeriana 6x, Aconitum nap. 15x, Apis mel. 15x, Arnica 15x, Arsenicum alb. 15x, Belladonna 15x, Bellis 15x, Bryonia 15x, Calendula 15x, Chamomilla 15x, Cistus canadensis 15x, Ferrum phosphoricum 15x, Histaminum hydrochloricum 15x, Hypericum 15x, Ignatia 15x, Mezereum 15x, Ornithogalum 15x, Passiflora 15x, Phosphorus 15x, Prunus spin. 15x, Rhus toxicodendron 15x, Sarcolacticum ac. 15x, Sulphur 15x, Veratrum alb. 15x.

OTC - PURPOSE SECTION

Formulated for symptoms such as fellings of panic, anxiety, tension or fear.

INACTIVE INGREDIENT SECTION

Inactive Ingredients: USP Purified Water; USP Gluten-free, non-GMO, organic cane alcohol 20%.

QUESTIONS SECTION

newtonlabs.net – Questions? 800.448.7256

Newton Laboratories, Inc. FDA Est # 1051203 - Conyers, GA 30013

WARNINGS SECTION

WARNINGS: Keep out of reach of children. Do not use if tamper-evident seal is broken or missing. If symptoms worsen or persist for more than a few days, consult a doctor. If pregnant or breast-feeding, ask a doctor before use.

OTC - PREGNANCY OR BREAST FEEDING SECTION

If pregnant or breast-feeding, ask a doctor before use.

OTC - KEEP OUT OF REACH OF CHILDREN SECTION

Keep out of reach of children.